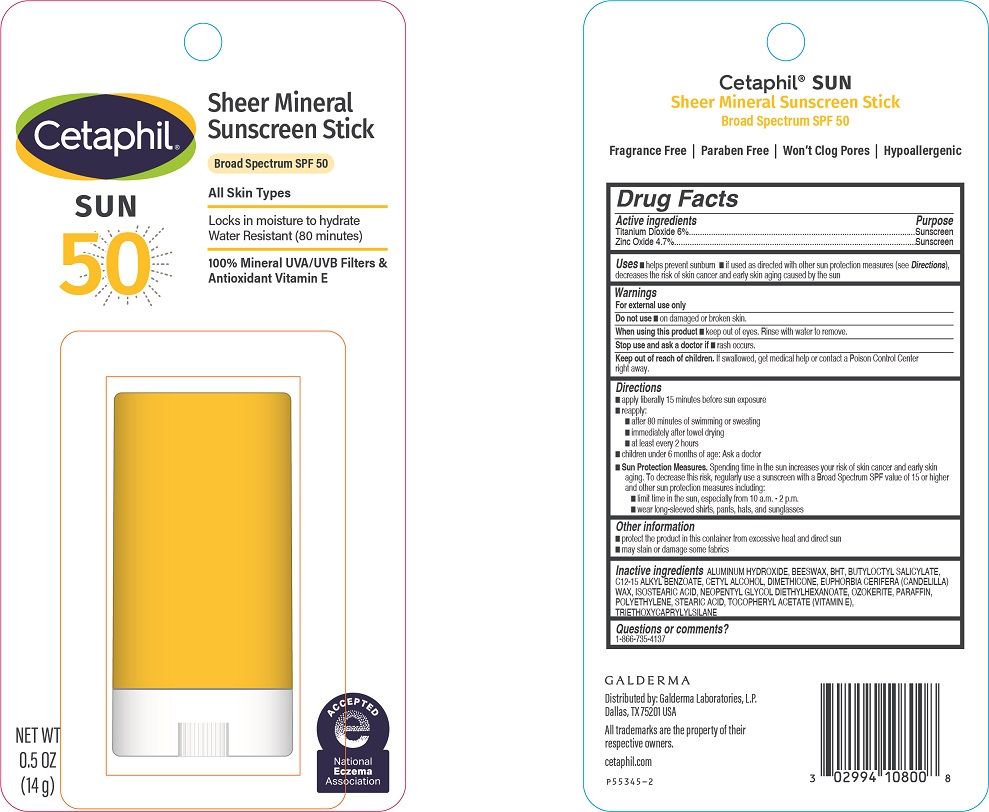 DRUG LABEL: Cetaphil Sheer Mineral Sunscreen Stick SPF 50
NDC: 0299-4108 | Form: STICK
Manufacturer: Galderma Laboratories, L.P.
Category: otc | Type: HUMAN OTC DRUG LABEL
Date: 20250127

ACTIVE INGREDIENTS: Titanium Dioxide 60 mg/1 g; Zinc Oxide 47 mg/1 g
INACTIVE INGREDIENTS: Aluminum Hydroxide; Yellow Wax; Butylated Hydroxytoluene; Butyloctyl Salicylate; Alkyl (C12-15) Benzoate; Cetyl Alcohol; Dimethicone; Candelilla Wax; Isostearic Acid; Neopentyl Glycol Diethylhexanoate; Ceresin; Paraffin; High Density Polyethylene; Stearic Acid; .Alpha.-Tocopherol Acetate, D-; Triethoxycaprylylsilane

Cetaphil Sheer Mineral Sunscreen Stick Broad Spectrum SPF 50

Active Ingredients

Titianium Dioxide 6%
Zinc Oxide 4.7%

Purpose

Sunscreen

Uses

- helps prevent sunburn
- if used as directed with other sun protection measures (see Directions), decreases the risk of skin cancer and early skin aging caused by the sun

Do not use

▪ on damaged or broken skin

When using this product

• keep out of eyes. Rinse with water to remove.

Stop use and ask a doctor if

• rash occurs.

Keep out of reach of children.

If swallowed, get medical help or contact a Poison Control Center right away.

Directions

- apply liberally 15 minutes before sun exposure
- reapply:
  - after 80 minutes of swimming or sweating
  - immediately after towel drying
  - at least every 2 hours
- children under 6 months of age: Ask a doctor
- Sun Protection Measures. Spending time in the sun increases your risk of skin cancer and early skin aging. To decrease this risk, regularly use a sunscreen with a Broad Spectrum SPF value of 15 or higher and other sun protection measures including:
  - limit time in the sun, especially from 10 a.m. - 2 p.m.
  - wear long-sleeved shirts, pants, hats, and sunglasses

Other Information
▪ protect the product in this container from excessive heat and direct sun
▪ may stain or damage some fabrics

Inactive Ingredients

ALUMINUM HYDROXIDE, BEESWAX, BHT, BUTYLOCTYL SALICYLATE, C12-15 ALKYL BENZOATE, CETYL ALCOHOL, DIMETHICONE, EUPHORBIA CERIFERA (CANDELILLA) WAX, ISOSTEARIC ACID, NEOPENTYL GLYCOL DIETHYLHEXANOATE, OZOKERITE, PARAFFIN, POLYETHYLENE, STEARIC ACID, TOCOPHERYL ACETATE (VITAMIN E), TRIETHOXYCAPRYLYLSILANE

Questions or comments?

1-866-735-4137

PRINCIPAL DISPLAY PANEL - 0.5 OZ Card

Cetaphil®

SUN

50

Sheer Mineral Sunscreen Stick

Broad Spectrum SPF 50
All Skin Types
Locks in moisture to hydrate
Water resistant (80 minutes)
100% Mineral UVA/UVB Filters &
Antioxidant Vitamin E
NET WT 0.5 OZ (14 g)
National Eczema Association logo

Distributed by:
Galderma Laboratories, L.P.
Dallas, TX 75201 USA
All trademarks are the property of their respective owners
cetaphil.com
P55345-2